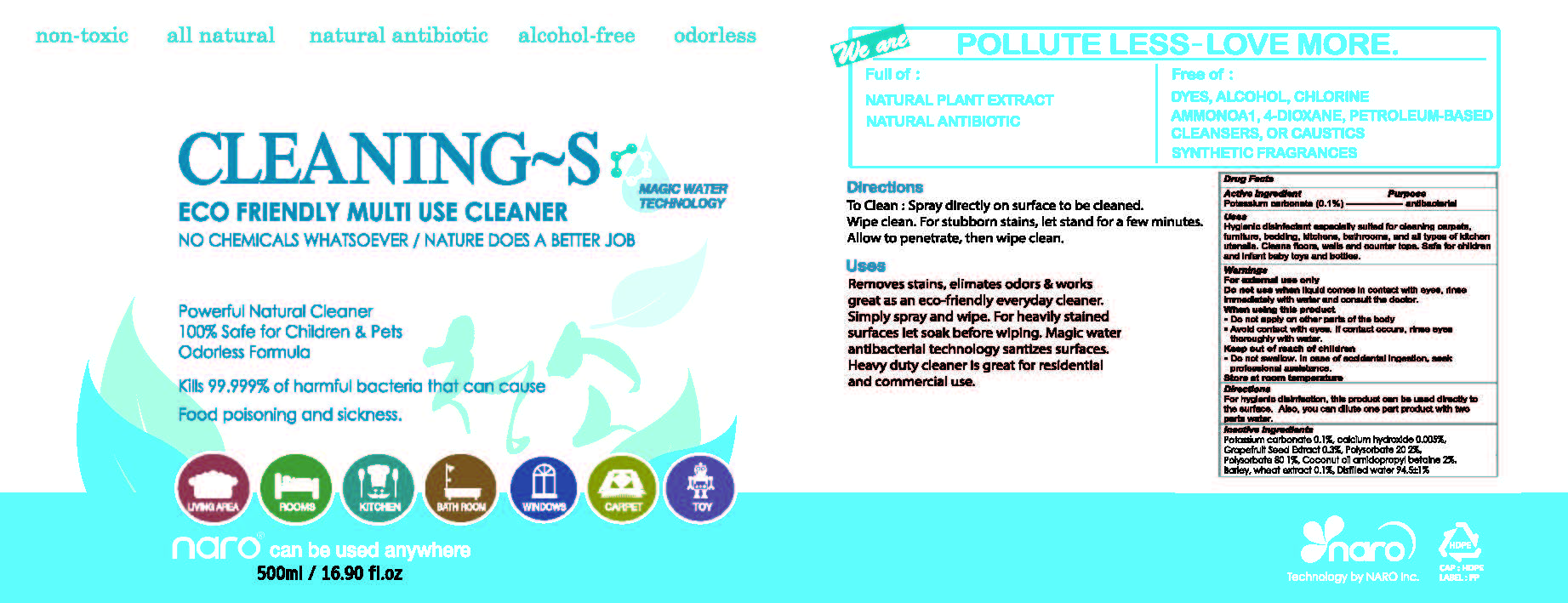 DRUG LABEL: CLEANING-S
NDC: 71957-0001 | Form: LIQUID
Manufacturer: NARO, INC.
Category: otc | Type: HUMAN OTC DRUG LABEL
Date: 20180101

ACTIVE INGREDIENTS: POTASSIUM CARBONATE 0.1 g/100 mL
INACTIVE INGREDIENTS: POLYSORBATE 20; POLYSORBATE 80; COCONUT OIL

ACTIVE INGREDIENT

Potassium carbonate

INACTIVE INGREDIENT

Polysorbate20, Polysorbate80, Coconut oil, etc

PURPOSE

Antibacterial

Keep out of reach of children
 Do not swallow. In case of accidental ingestion, seek professional assistance.

INDICATIONS AND USAGE

Hygienic disinfectant especially suited for cleaning carpets, furniture, bedding, kitchens, bathrooms, and all types of kitchen utensils. Cleans floors, walls and counter tops. Safe for children and infant baby toys and bottles.

Warnings
For external use only
Do not use when liquid comes in contact with eyes, rinse immediately with water and consult the doctor.
When using this product

- Do not apply on other parts of the body
- Avoid contact with eyes. If contact occurs, rinse eyes thoroughly with water.

Store at room temperature

Directions
For hygienic disinfection, this product can be used directly to the surface. Also, you can dilute one part product with two parts water.